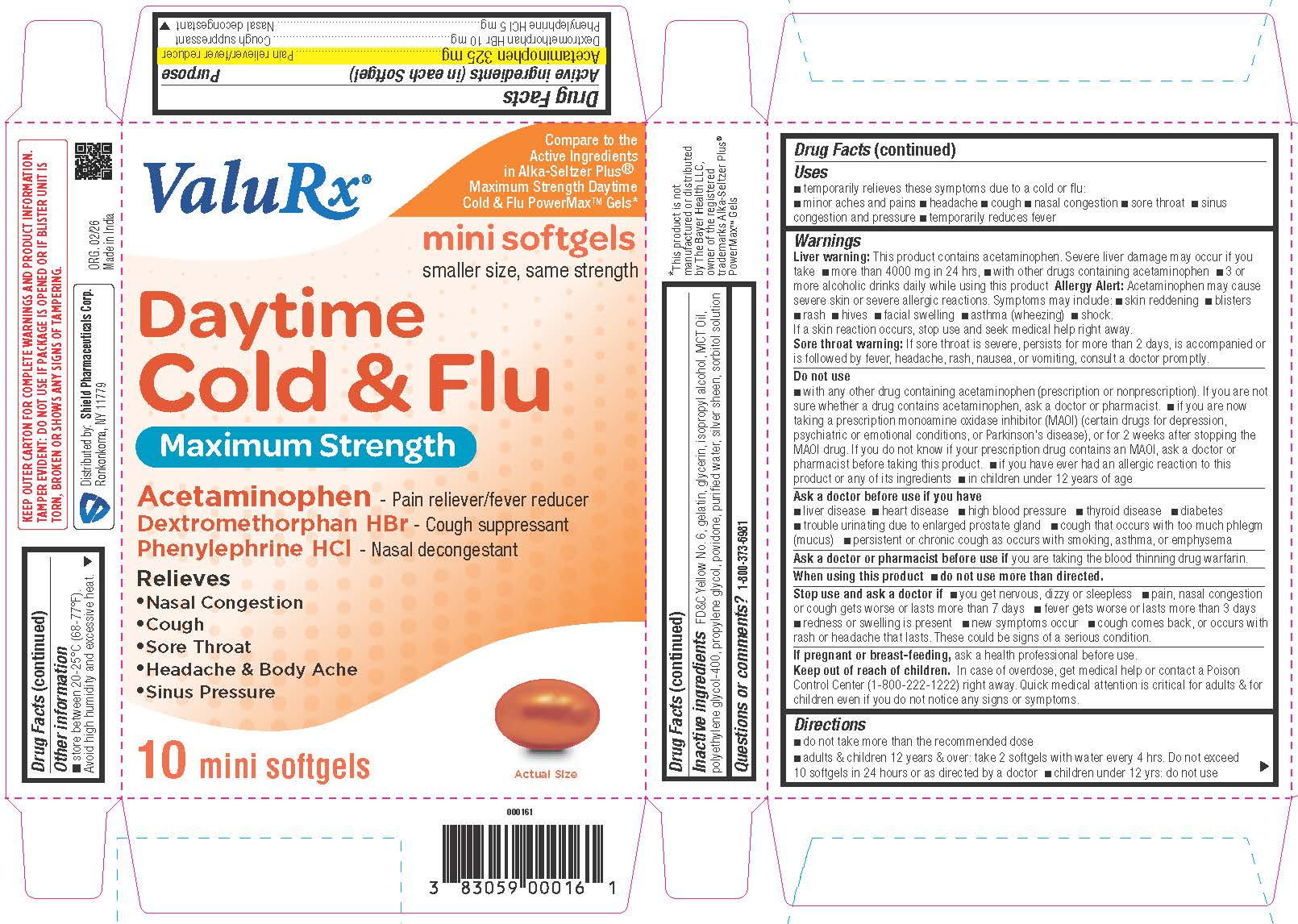 DRUG LABEL: Daytime Cold and Flu mini Softgels
NDC: 83059-0050 | Form: CAPSULE, LIQUID FILLED
Manufacturer: Shield Pharmaceuticals Corp
Category: otc | Type: HUMAN OTC DRUG LABEL
Date: 20260224

ACTIVE INGREDIENTS: ACETAMINOPHEN 325 mg/1 1; DEXTROMETHORPHAN HYDROBROMIDE 10 mg/1 1; PHENYLEPHRINE HYDROCHLORIDE 5 mg/1 1
INACTIVE INGREDIENTS: BUTYLATED HYDROXYANISOLE; FD&C YELLOW NO. 6; GELATIN; GLYCERIN; METHYLPARABEN; POLYETHYLENE GLYCOL 400; PROPYLENE GLYCOL; PROPYLPARABEN; POVIDONE; SORBITOL; WATER

Daytime Cold and Flu mini Softgels

Drug Facts

Active ingredient (in each softgel)

Acetaminophen 325 mg
Dextromethorphan HBr 10 mg
Phenylephrine HCl 5 mg

Purpose

Pain reliever/fever reducer
Cough suppressant
Nasal decongestant

Uses

temporarily relieves common cold/flu symptoms:
• nasal congestion
• cough due to minor
• throat & bronchial irritation
• sore throat
• headache
• minor aches & pains
• fever

Warnings

Liver warning:This product contains acetaminophen. Severe liver damage may occur if you take
• more than 10 Softgels in 24 hrs, which is the maximum daily amount for this product
• with other drugs containing acetaminophen
• 3 or more alcoholic drinks daily while using this product
Allergy Alert:Acetaminophen may cause severe skin reactions. Symptoms may
• include:
• skin reddening
• blisters
• rash

If a skin reaction occurs, stop use and seek medical help right away.
Sore throat warning:If sore throat is severe, persists for more than 2 days, is accompanied or is followed by fever, headache, rash, nausea, or vomiting, consult a doctor promptly.

Do not use

• with any other drug containing acetaminophen (prescription or nonprescription). If you are
• not sure whether a drug contains acetaminophen, ask a doctor or pharmacist.
• if you are now taking a prescription monoamine oxidase inhibitor (MAOI) (certain drugs for depression, psychiatric or emotional conditions, or Parkinson's disease), or for 2 weeks after stopping the MAOI drug. If you do not know if your prescription drug contains an MAOI, ask a doctor or pharmacist before taking this product.

Ask a doctor before use if you have
• liver disease
• heart disease
• high blood pressure
• thyroid disease
• diabetes
• trouble urinating due to enlarged prostate gland
• cough that occurs with too much phlegm (mucus)
• persistent or chronic cough as occurs with smoking, asthma, or emphysema

Ask a doctor or pharmacist before use if you are taking the blood thinning drug warfarin.

When using this product
• do not use more than directed.

Stop use and ask a doctor if
• you get nervous, dizzy or sleepless
• pain, nasal congestion or cough gets worse or lasts more than 7 days
• fever gets worse or lasts more than 3 days
• redness or swelling is present
• new symptoms occur
• cough comes back, or occurs with rash or headache that lasts.

PREGNANCY OR BREAST FEEDING

If pregnant or breast-feeding,ask a health professional before use.

Keep out of reach of children.In case of overdose, get medical help or contact a Poison Control Center (1-800-222-1222) right away. Quick medical attention is critical for adults & for children even if you do not notice any signs or symptoms.

Directions

take only as directed do not exceed 8 softgels per 24 hrs

adults & children 12 yrs & over | 2 Softgels with water every 4 hrs
children 4 to under 12 yrs | ask a doctor
children under 4 yrs | do not use

Other information

• store between 20-25°C (68-77°F).
Avoid high humidity and excessive heat.
Protect from light.

Questions or comments?

1-800-373-6981 (toll-free)

Inactive ingredients

FD&C Yellow No. 6, gelatin, glycerin, isopropyl alcohol, MCT Oil, polyethylene glycol-400, propylene glycol, povidone, purified water,
silver sheen, sorbitol solution

Distributed by:
Shield Pharmaceuticals Corp.
Ronkonkoma, NY 11779

PRINCIPAL DISPLAY PANEL

DaytimeCold & Flu minin Softgels

Maximum Strength

Carton